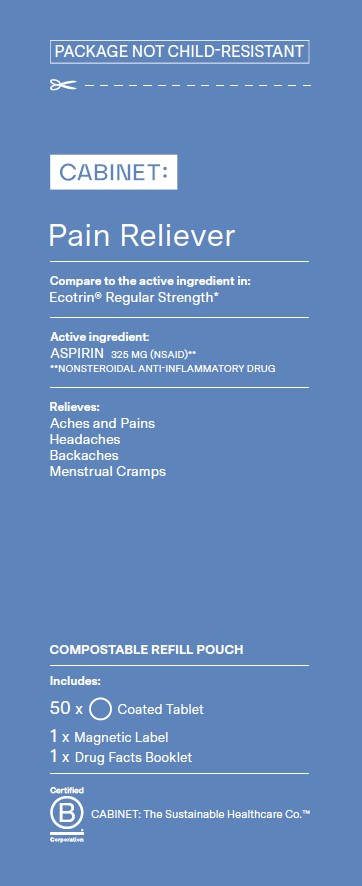 DRUG LABEL: Pain Reliever
NDC: 68210-4178 | Form: TABLET, COATED
Manufacturer: Spirit Pharmaceuticals LLC
Category: otc | Type: HUMAN OTC DRUG LABEL
Date: 20241212

ACTIVE INGREDIENTS: ASPIRIN 325 mg/1 1
INACTIVE INGREDIENTS: STARCH, CORN; CROSCARMELLOSE SODIUM; D&C YELLOW NO. 10; FD&C YELLOW NO. 6; HYPROMELLOSES; METHACRYLIC ACID; METHACRYLIC ACID - ETHYL ACRYLATE COPOLYMER (1:2); MICROCRYSTALLINE CELLULOSE; MINERAL OIL; POLYSORBATE 80; DIMETHICONE; SODIUM HYDROXIDE; SODIUM LAURYL SULFATE; TALC; TITANIUM DIOXIDE; TRIETHYL CITRATE

Pain Reliever

Active Ingredient (in each tablet)

Aspirin 325 mg (NSAID)**
**nonsteroidal anti-inflammatory drug

Purpose

Pain reliever

Uses

temporarily relieves minor aches and pains due to: • headache • minor arthritis pain • toothache • menstrual pain • colds • or as recommended by a doctor

Warnings

Reye’s syndrome: Children and teenagers who have or are recovering from chicken pox or flu-like symptoms should not use this product. When using this product, if changes in behavior with nausea and vomiting occur, consult a doctor because these symptoms could be an early sign of Reye’s syndrome, a rare but serious illness.
Allergy alert: Aspirin may cause a severe allergic reaction which may include: • hives • shock • facial swelling • asthma (wheezing)

Stomach bleeding warning: This product contains an NSAID, which may cause severe stomach bleeding. The chance is higher if you • are age 60 or older • have had stomach ulcers or bleeding problems • take a blood thinning (anticoagulant) or steroid drug • take other drugs containing prescription or nonprescription NSAIDs (aspirin, ibuprofen, naproxen, or others) • have 3 or more alcoholic drinks every day while using this product • take more or for a longer time than directed

Do not use

if you have ever had an allergic reaction to aspirin or any other pain reliever/fever reducer

Ask a doctor before use if you

• stomach bleeding warning applies to you • you have a history of stomach problems, such as heartburn • you have high blood pressure, heart disease, liver cirrhosis, or kidney disease • you are taking a diuretic • you have asthma

Ask a doctor or pharmacist before use if you are

if you are taking a prescription drug for diabetes, gout, or arthritis

Stop use and ask a doctor if

• an allergic reaction occurs. Seek medical help right away. • you experience any of the following signs of stomach bleeding: • feel faint • vomit blood • have bloody or black stools • fever gets worse or lasts for more than 3 days • have stomach pain that does not get better • pain gets worse or lasts more than 10 days • redness or swelling is present • any new symptoms appear • ringing in the ears or a loss of hearing occurs. These could be signs of a serious condition.

If pregnant or breast-feeding,

ask a health professional before use. It is especially important not to use aspirin during the last 3 months of pregnancy unless definitely directed to do so by a doctor because it may cause problems in the unborn child or complications during delivery.

Keep out of reach of children.

In case of overdose, get medical help or contact a Poison Control Center right away (1-800-222-1222).

Directions

• adults and children 12 years of age and over: take 1 to 2 tablets every 4 hours, while symptoms persist. Drink a full glass of water with each dose.
• do not take more than 12 tablets in 24 hours unless directed by a doctor
• children under 12 years of age: ask a doctor

Other information

• store between 20–25°C (68–77°F)

Inactive ingredients

Corn starch, croscarmellose sodium, D&C Yellow No. 10 Aluminum Lake, FD&C Yellow No. 6 Aluminum Lake, hypromellose, methacrylic acid copolymer, microcrystalline cellulose, mineral oil, polysorbate 80, simethicone, sodium hydroxide, sodium lauryl sulfate, talc, titanium dioxide, triethyl citrate

Questions or comments?

1-888-333-9792

Distributed by:

Cabinet Health P.B.C.